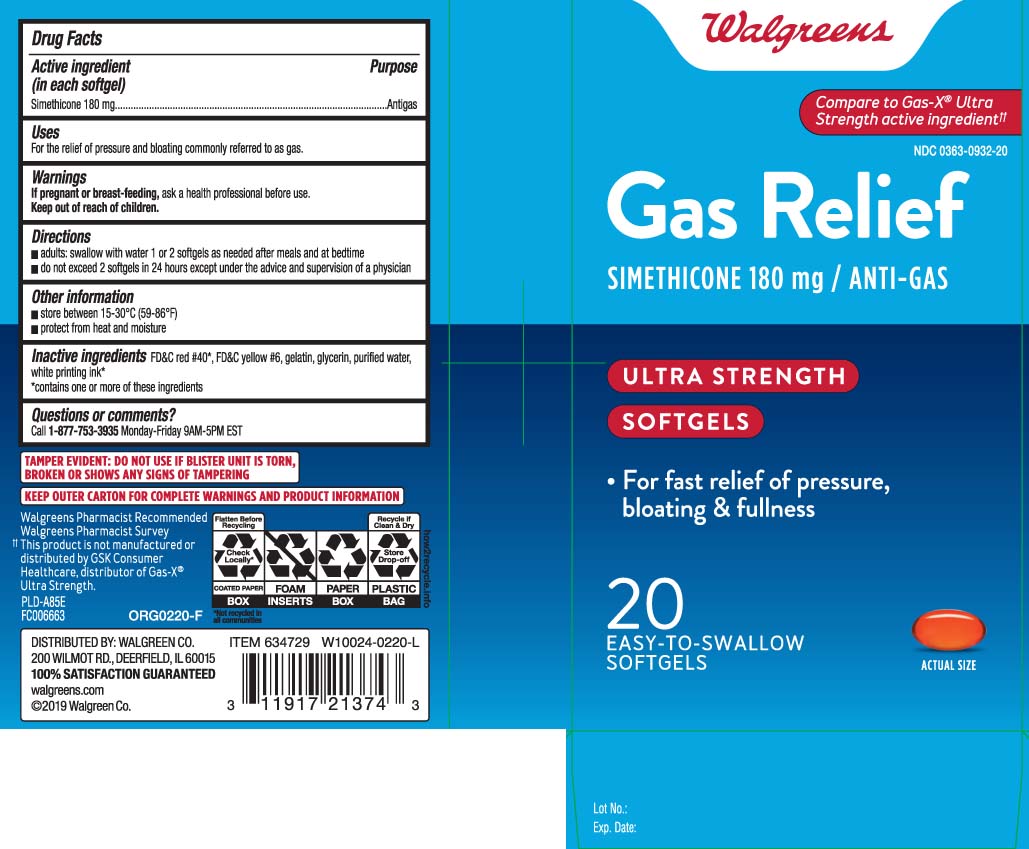 DRUG LABEL: Gas Relief
NDC: 0363-0932 | Form: CAPSULE, LIQUID FILLED
Manufacturer: Walgreens
Category: otc | Type: HUMAN OTC DRUG LABEL
Date: 20240626

ACTIVE INGREDIENTS: DIMETHICONE 180 mg/1 1
INACTIVE INGREDIENTS: FD&C YELLOW NO. 6; GELATIN; GLYCERIN; WATER; FD&C RED NO. 40

Drug Facts

Active ingredient (in each softgel)

Simethicone 180 mg

Purpose

Antiflatulent (Antigas)

Uses

- relieves bloating, pressure, or fullness commonly referred to as gas

Warnings

Stop use and ask a doctor if

condition persists.

If pregnant or breast-feeding,

ask a health professional before use.

Directions

- swallow one or two softgels as needed after meals
- do not exceed two softgels per day except under the advice and supervision of a physician

Other information

- store between 15-30ºC (59-86ºF)
- protect from heat and moisture

Inactive ingredients

FD&C red #40*, FD&C yellow #6, gelatin, glycerin, purified water, white printing ink*

*contains one or more of these ingredients

Questions or comments?

Call 1-877-753-3935 Monday-Friday 9AM-5PM EST

Principal Display Panel

Compare to Phazyme® Ultra Strength active ingredient††

Gas Relief

SIMETHICONE 180 mg / ANTI-GAS

ULTRA STRENGTH

SOFTGELS

- Relieves bloating, gas, pressure & discomfort

SOFTGELS

EASY-TO-SWALLOW SOFTGELS

††This product is not manufactured or distributed by C.B. Fleet Company Inc., distributor of Phazyme® Ultra Strength

TAMPER EVIDENT: DO NOT USE IF PRINTED SAFETY SEAL UNDER CAP IS BROKEN OR MISSING

KEEP OUTER CARTON FOR COMPLETE WARNINGS AND PRODUCT INFORMATION.

DISTRIBUTED BY: WALGREEN CO.

200 WILMOT RD., DEERFIELD, IL 60015

Product Label

WALGREENS Gas Relief